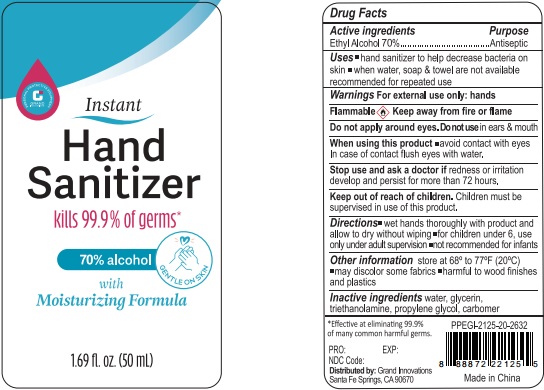 DRUG LABEL: Instant Hand Sanitizer
NDC: 52174-202 | Form: GEL
Manufacturer: Ningbo BST Clean And Care Products Co., Ltd
Category: otc | Type: HUMAN OTC DRUG LABEL
Date: 20200419

ACTIVE INGREDIENTS: alcohol 70 mL/100 mL
INACTIVE INGREDIENTS: WATER; PROPYLENE GLYCOL; TROLAMINE; GLYCERIN

Drug facts

Active ingredient Purpose

Ethyl Alcohol 70% ... Antiseptic

PURPOSE

- Hand sanitizer to help decrease bacteria on the skin.
- When water, soap and towel are not available, recommended for repeated use.

KEEP OUT OF REACH OF CHILDREN

Children must be supervised in use of this product.

INDICATIONS AND USAGE

keep out of eyes

when water, soap and towel are not available

WARNINGS

For external use only: hands
Flammable. Keep away from fire or flame.

Do not apply around eyes; Do not use in ears and mouth.

When using this products, avoid contact with eyes. In case of contact, flush eyes with water.

Stop using and ask a doctor, if redness and irritation develop and persist for more than 72 hours.

OTHER INFORMATION: store at 68° - 77℉ （20℃).

- may discolor some fabrics
- harmful to wood finished and plastics

DOSAGE AND ADMINISTRATION

- wet hands thorougjly with product and allow to dry without wiping.
- For Children under 6, use only under adult supervision.
- not recommended for infants.

INACTIVE INGREDIENT

Water, Glycerin, trithanolamine, propylene glycol, carbomer